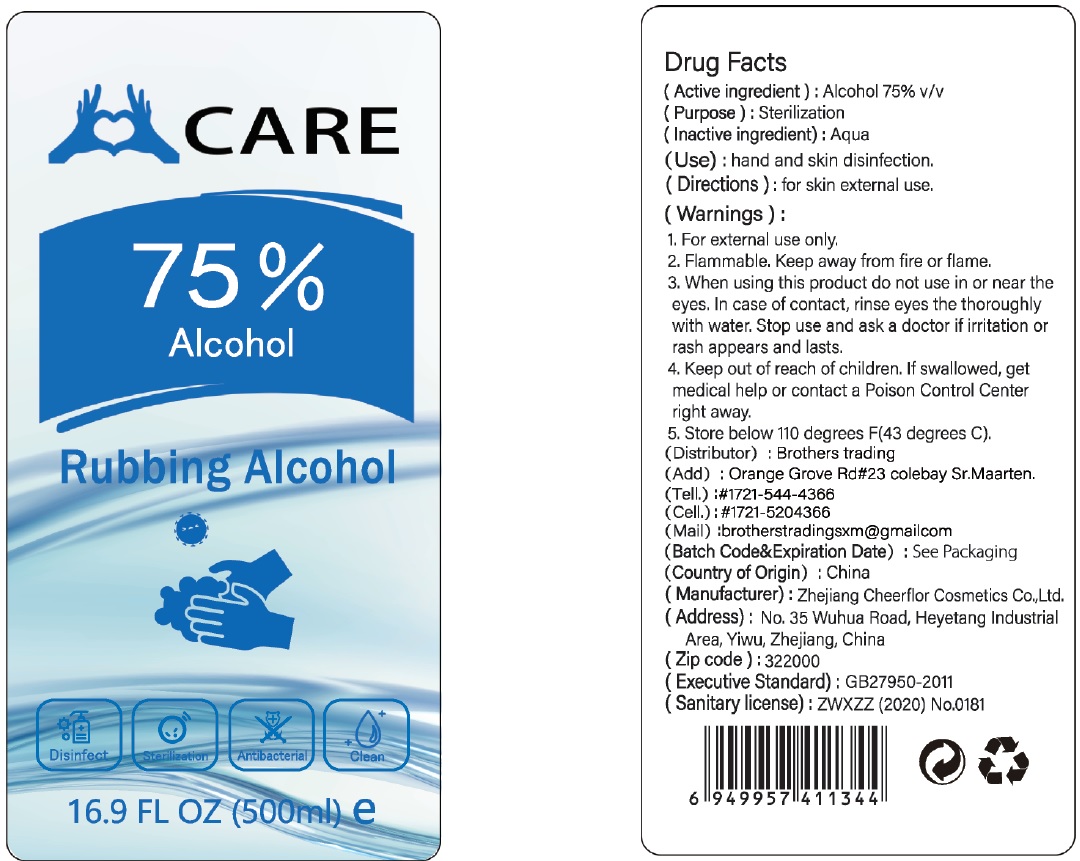 DRUG LABEL: Rubbing Alcohol
NDC: 78163-002 | Form: GEL
Manufacturer: Zhejiang Cheerflor Cosmetics Co., Ltd.
Category: otc | Type: HUMAN OTC DRUG LABEL
Date: 20201006

ACTIVE INGREDIENTS: ALCOHOL 0.75 mL/1 mL
INACTIVE INGREDIENTS: WATER

Rubbing Alcohol

(Active ingredient):

Alcohol 75% v/v

(Purpose):

Sterilization

(Inactive ingredient):

Aqua

(Use):

hand and skin disinfection.

(Directions):

for skin external use.

(Warnings):

For external use only.

Flammable. Keep away from fire or flame.

When using this product

do not use in or near the eyes. In case of contact, rinse eyes the thoroughly with water.

Stop use and ask a doctor

if irritation or rash appears and lasts.

Keep out of reach of children.

If swallowed, get medical help or contact a Poison Control Center right away.

Store below 110 degrees F(43 degrees C).